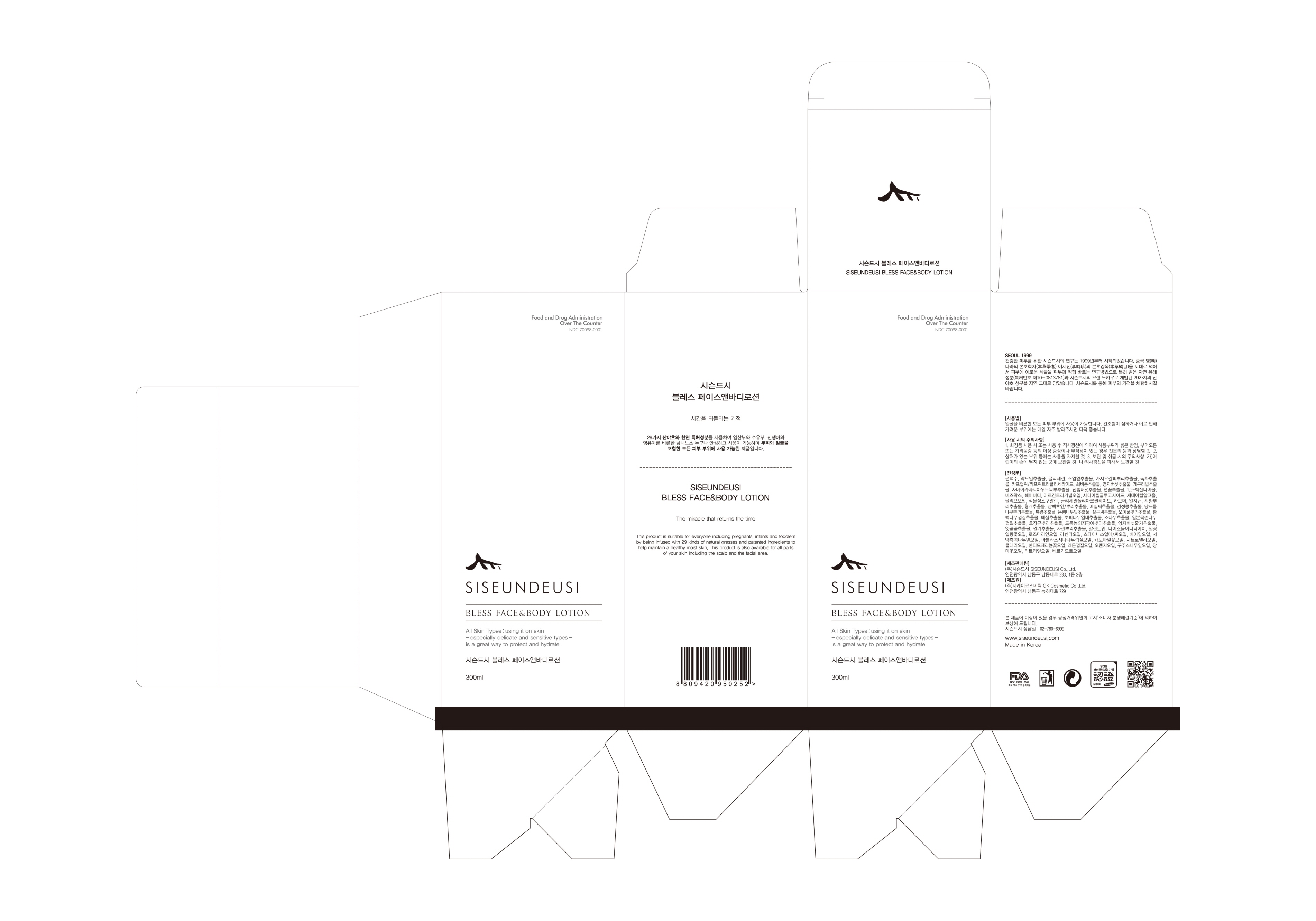 DRUG LABEL: SISEUNDEUSI BLESS FACE and BODY
NDC: 70098-0016 | Form: LOTION
Manufacturer: GK COSMETIC CO., LTD.
Category: otc | Type: HUMAN OTC DRUG LABEL
Date: 20181206

ACTIVE INGREDIENTS: GLYCERIN 5.75 g/100 mL
INACTIVE INGREDIENTS: ALLANTOIN; SHEA BUTTER

Drug Facts

ACTIVE INGREDIENT

GLYCERIN

INACTIVE INGREDIENT

Chamaecyparis Obtusa Water, Houttuynia Cordata Extract, Butyrospermum Parkii (Shea Butter), Allantoin, etc.

PURPOSE

SKIN PROTECTANT

keep out of reach of the children

INDICATIONS AND USAGE

All body area is applicable. It is better if you apply it frequently every day to the dried and, therefore itchy areas. It is applicable to all the area of skin.

WARNINGS

1. Do not use in the following cases(Eczema and scalp wounds)
2.Side Effects
1)Due to the use of this druf if rash, irritation, itching and symptopms of hypersnesitivity occur dicontinue use and consult your phamacisr or doctor
3.General Precautions
1)If in contact with the eyes, wash out thoroughty with water If the symptoms are servere, seek medical advice immediately
2)This product is for exeternal use only. Do not use for internal use
4.Storage and handling precautions
1)If possible, avoid direct sunlight and store in cool and area of low humidity
2)In order to maintain the quality of the product and avoid misuse
3)Avoid placing the product near fire and store out in reach of children

DOSAGE AND ADMINISTRATION

for external use only